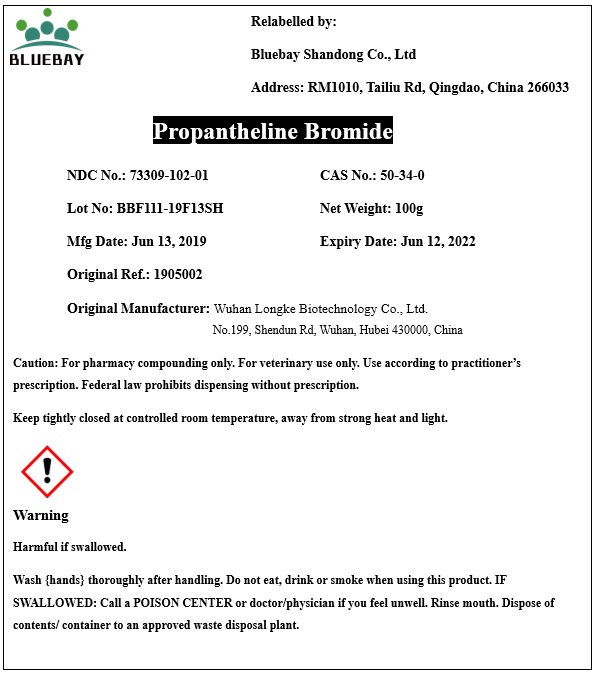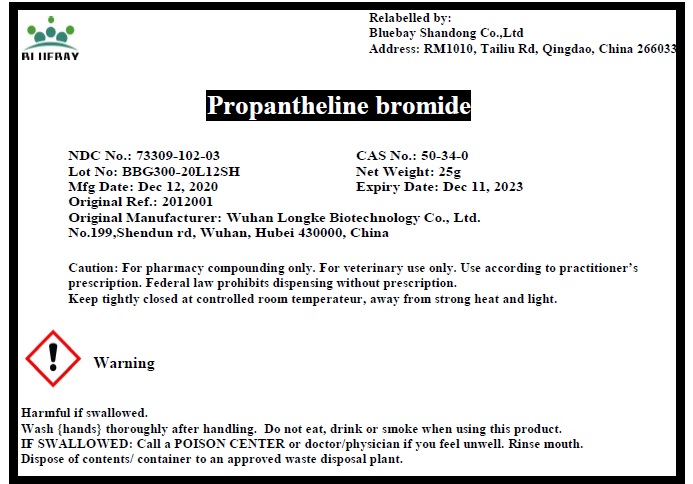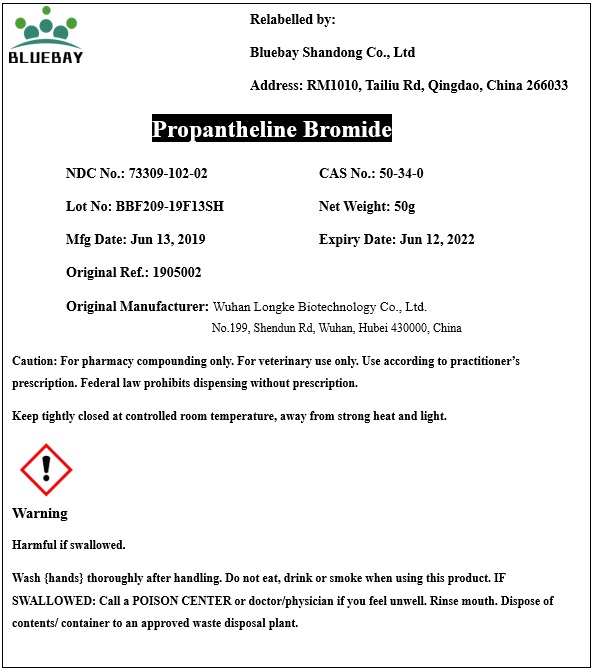 DRUG LABEL: Propantheline Bromide
NDC: 73309-102 | Form: POWDER
Manufacturer: BLUEBAY SHANDONG CO.,LTD
Category: other | Type: BULK INGREDIENT
Date: 20210609

ACTIVE INGREDIENTS: PROPANTHELINE BROMIDE 1 g/1 g

Propantheline Bromide